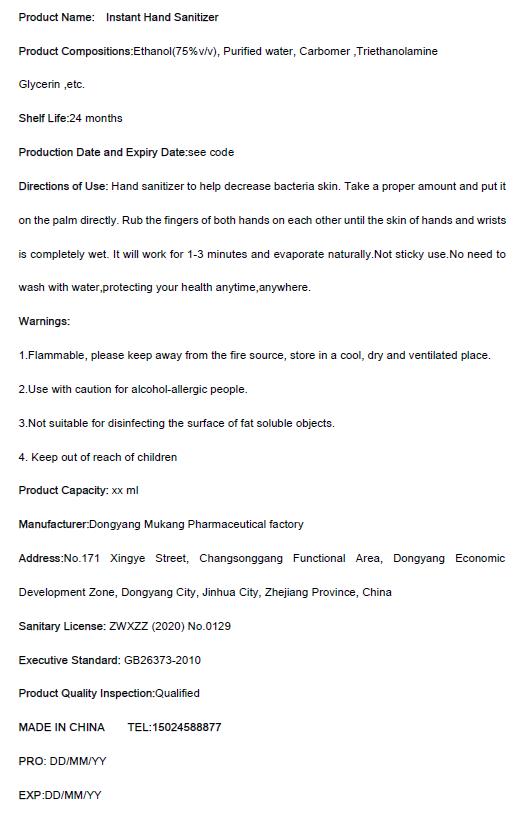 DRUG LABEL: Instant Hand Sanitizer
NDC: 75586-101 | Form: GEL
Manufacturer: Dongyang Mukang Pharmaceutical Factory
Category: otc | Type: HUMAN OTC DRUG LABEL
Date: 20200505

ACTIVE INGREDIENTS: ALCOHOL 75 mL/100 mL
INACTIVE INGREDIENTS: GLYCERIN; WATER; CARBOMER HOMOPOLYMER, UNSPECIFIED TYPE; TROLAMINE

Mukang, Hand Sanitizer, 75% Ethanol, Gel, xx mL

Active Ingredient(s)

Ethanol 75% v/v. Purpose: Antiseptic

Purpose

Hand sanitizer to help decrease bacteria skin.

Use

Take a proper amount and put it on the palm directly. Rub the fingers of both hands on each other until the skin of hands and wrists is completely wet. It will work for 1-3 minutes and evaporate naturally. Not sticky use. No need to wash with water, protecting your health anytime, anywhere.

Warnings

1. Flammable, please keep away from the fire source, store in a cool, dry and ventilated place.
2. Use with caution for alcohol-allergic people.
3. Not suitable for disinfecting the surface of fat soluble objects.
4. Keep out of reach of children.

Do not use

1. Not sticky use.

2. Use with caution for alcohol-allergic people.
3. Not suitable for disinfecting the surface of fat soluble objects.

WHEN USING

This product is for external use, no taken orally, avoid contact with eyes.

STOP USE

If there is skin irritation, please stop using. If further irritation, please consult a doctor and keep it below.

Keep away from reach of children.

Directions

Take a proper amount and put it on the palm directly. Rub the fingers of both hands on each other until the skin of hands and wrists is completely wet. It will work for 1-3 minutes and evaporate naturally. Not sticky use. No need to wash with water, protecting your health anytime, anywhere.

Other information

Store at a cool place, avoid sunlight.

Inactive ingredients

Purified water, Triethanolamine, Glycerin, Carbomer.